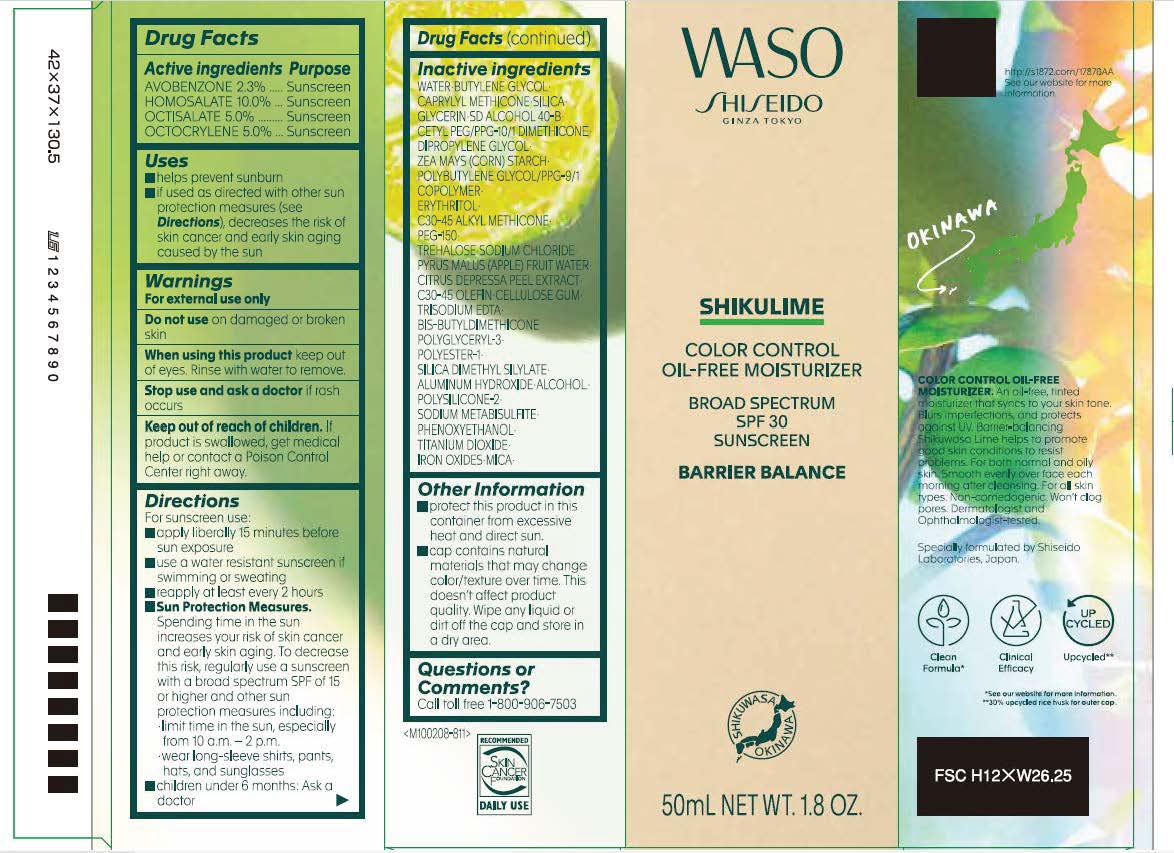 DRUG LABEL: SHISEIDO WASO SHIKULIME COLOR CONTROL
NDC: 58411-965 | Form: CREAM
Manufacturer: Shiseido Americas Corporation
Category: otc | Type: HUMAN OTC DRUG LABEL
Date: 20260206

ACTIVE INGREDIENTS: AVOBENZONE 1.24959 g/50 mL; HOMOSALATE 5.433 g/50 mL; OCTISALATE 2.7165 g/50 mL; OCTOCRYLENE 2.7165 g/50 mL
INACTIVE INGREDIENTS: WATER; BUTYLENE GLYCOL; CAPRYLYL METHICONE; SILICA; GLYCERIN; DIPROPYLENE GLYCOL; ZEA MAYS (CORN) STARCH; ERYTHRITOL; C30-45 ALKYL METHICONE; PEG-150; TREHALOSE; SODIUM CHLORIDE; APPLE FRUIT OIL; TANGERINE PEEL; C30-45 OLEFIN; CELLULOSE GUM; TRISODIUM EDTA; SILICA DIMETHYL SILYLATE; ALUMINUM HYDROXIDE; ALCOHOL; SODIUM METABISULFITE; PHENOXYETHANOL; TITANIUM DIOXIDE; FERRIC OXIDE RED; MICA; CETYL PEG/PPG-10/1 DIMETHICONE (HLB 5)

SHISEIDO WASO SHIKULIME COLOR CONTROL

Drug Facts

Active Ingredients | Purpose
AVOBENZONE 2.3% | Sunscreen
HOMOSALATE 10% | Sunscreen
OCTISALATE 5.0% | Sunscreen
OCTOCRYLENE 5.0% | Sunscreen

Uses

- helps prevent sunburn
- if used as directed with other sun protection measures (see Directions), decreases the risk of skin cancer and early skin aging caused by the sun

Warnings

For external use only

Do not useon damaged or broken skin

WHEN USING

When using this productkeep out of eyes. Rinse with water to remove.

Stop use and ask a doctorif rash occurs

Keep out of reach of children. If product is swallowed, get medical help or contact a Poison Co

Directions

For suncreen use:

- apply liberally 15 minutes before sun exposure
- use a water resistant sun screen if swimming or sweating
- reapply at least every 2 hours
- Sun Protection Measures.Spending time in the sun increases your risk of skin cancer and early skin aging. To decrease this risk, regularly use a sunscreen with a broad spectrum SPF of 15 or higher and other sun protection measures including:

-limit time in the sun, especially from 10 a.m. - 2p.m.

-wear long-sleeve shirts, pant, hats, and sunglasses

- children under 6 months: Ask a doctor

Inactive Ingredients

WATER･BUTYLENE GLYCOL･CAPRYLYL METHICONE･SILICA･GLYCERIN･SD ALCOHOL 40-B･CETYL PEG/PPG-10/1 DIMETHICONE･DIPROPYLENE GLYCOL･ZEA MAYS (CORN) STARCH･POLYBUTYLENE GLYCOL/PPG-9/1 COPOLYMER･ERYTHRITOL･C30-45 ALKYL METHICONE･PEG-150･TREHALOSE･SODIUM CHLORIDE･PYRUS MALUS (APPLE) FRUIT WATER･CITRUS DEPRESSA PEEL EXTRACT･C30-45 OLEFIN･CELLULOSE GUM･TRISODIUM EDTA･BIS-BUTYLDIMETHICONE POLYGLYCERYL-3･POLYESTER-1･SILICA DIMETHYL SILYLATE･ALUMINUM HYDROXIDE･ALCOHOL･POLYSILICONE-2･SODIUM METABISULFITE･PHENOXYETHANOL･TITANIUM DIOXIDE･IRON OXIDES･MICA･

Other Information

- protect this product in this container fro excessive heat and direct sun.
- cap contains natural materials that may change color/texture over time. This doesn't affect product quality. Wipe any liquid or dirt off the cap and store in a dry area.

Questions or Comments?

Call toll free-1-800-906-7503

PRINCIPLE DISPLAY PANEL- 50 mL

WASO

SHISEIDO

GINZA TOKYO

SHIKULIME

COLOR CONTROL

OIL-FREE MOISTURIZER

BROAD SPECTRUM

SPF 30

SUNSCREEN

BARRIER BALANCE

50mL NET WT. 1.8 OZ.